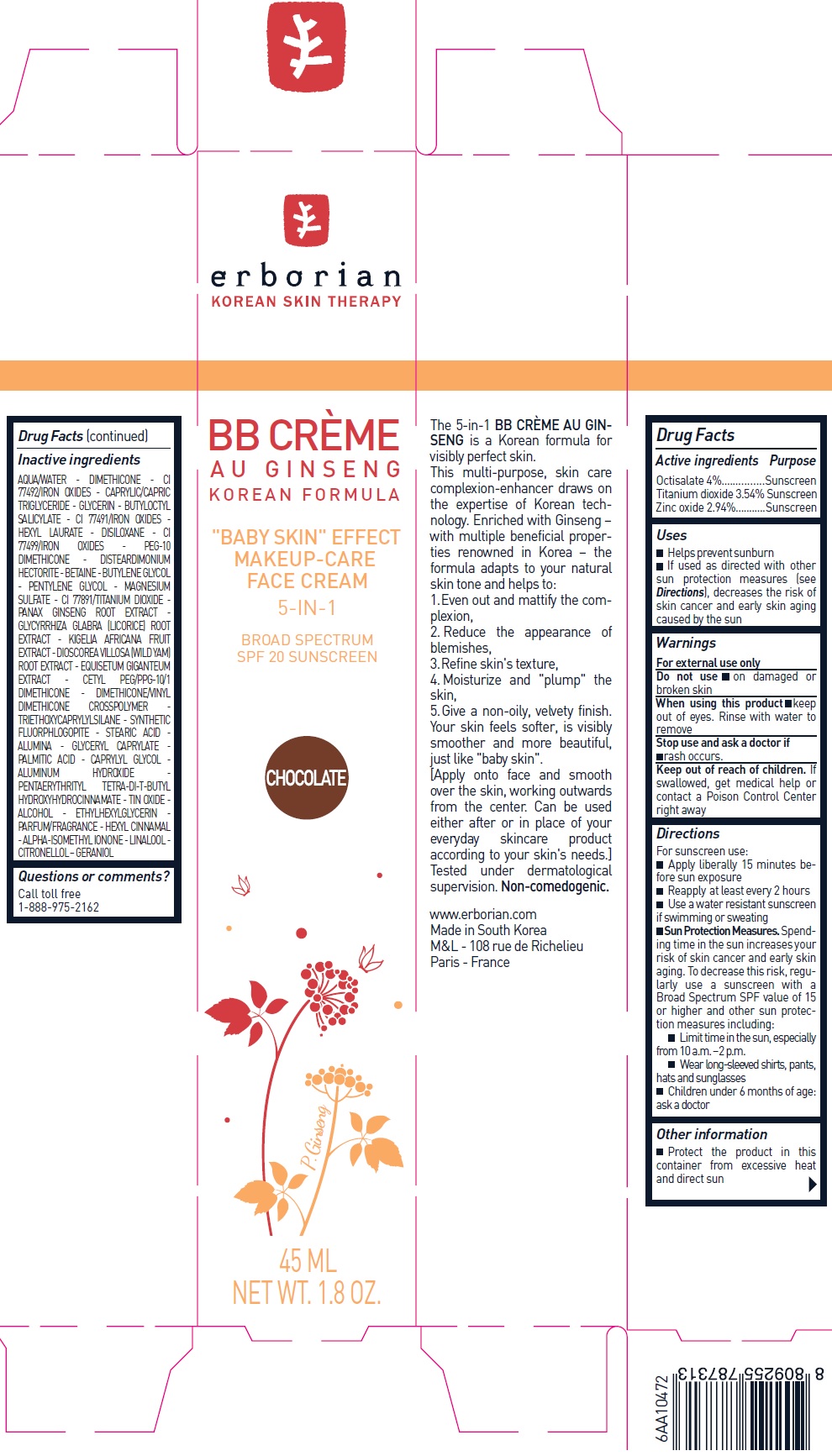 DRUG LABEL: Erborian BB creme au Ginseng chocolate SPF 20
NDC: 10345-904 | Form: CREAM
Manufacturer: LABORATOIRES M&L
Category: otc | Type: HUMAN OTC DRUG LABEL
Date: 20231209

ACTIVE INGREDIENTS: OCTISALATE 40 mg/1 mL; TITANIUM DIOXIDE 35.4 mg/1 mL; ZINC OXIDE 29.4 mg/1 mL
INACTIVE INGREDIENTS: WATER; DIMETHICONE; FERRIC OXIDE YELLOW; MEDIUM-CHAIN TRIGLYCERIDES; GLYCERIN; BUTYLOCTYL SALICYLATE; FERRIC OXIDE RED; HEXYL LAURATE; HEXAMETHYLDISILOXANE; FERROSOFERRIC OXIDE; DISTEARDIMONIUM HECTORITE; BETAINE; BUTYLENE GLYCOL; PENTYLENE GLYCOL; MAGNESIUM SULFATE, UNSPECIFIED FORM; ASIAN GINSENG; GLYCYRRHIZA GLABRA; KIGELIA AFRICANA FRUIT; DIOSCOREA VILLOSA TUBER; TRIETHOXYCAPRYLYLSILANE; STEARIC ACID; ALUMINUM OXIDE; GLYCERYL MONOCAPRYLATE; PALMITIC ACID; CAPRYLYL GLYCOL; ALUMINUM HYDROXIDE; PENTAERYTHRITOL TETRAKIS(3-(3,5-DI-TERT-BUTYL-4-HYDROXYPHENYL)PROPIONATE); STANNIC OXIDE; ALCOHOL; ETHYLHEXYLGLYCERIN; .ALPHA.-HEXYLCINNAMALDEHYDE; ISOMETHYL-.ALPHA.-IONONE; LINALOOL, (+/-)-; .BETA.-CITRONELLOL, (R)-; GERANIOL

Erborian BB creme au Ginseng chocolate SPF 20

Active ingredients

Octisalate 4%

Titanium dioxide 3.54%

Zinc oxide 2.94%

Purpose

Sunscreen

Uses

- Helps prevent sunburn
- If used as directed with other sun protection measures (see), decreases the risk of skin cancer and early skin aging caused by the sun Directions

Warnings

For external use only

Do not use

- on damaged or broken skin

When using this product

keep out of eyes. Rinse with water to remove

Stop use and ask a doctor if

- rash occurs.

Keep out of reach of children.

If swallowed, get medical help or contact a Poison Control Center right away

Directions

For sunscreen use:

- Apply liberally 15 minutes before sun exposure
- Reapply at least every 2 hours
- Use a water resistant sunscreen if swimming or sweating
- Spending time in the sun increases your risk of skin cancer and early skin aging. To decrease this risk, regularly use a sunscreen with a Broad Spectrum SPF value of 15 or higher and other sun protection measures including: Sun Protection Measures.
- Limit time in the sun, especially from 10 a.m. –2 p.m.
- Wear long-sleeved shirts, pants, hats and sunglasses
- Children under 6 months of age: ask a doctor

Other information

- Protect the product in this container from excessive heat and direct sun

Inactive ingredients

AQUA/WATER - DIMETHICONE - CI 77492/IRON OXIDES - CAPRYLIC/CAPRIC TRIGLYCERIDE - GLYCERIN - BUTYLOCTYL SALICYLATE - CI 77491/IRON OXIDES - HEXYL LAURATE - DISILOXANE - CI 77499/IRON OXIDES - PEG-10 DIMETHICONE - DISTEARDIMONIUM HECTORITE - BETAINE - BUTYLENE GLYCOL - PENTYLENE GLYCOL - MAGNESIUM SULFATE - CI 77891/TITANIUM DIOXIDE - PANAX GINSENG ROOT EXTRACT - GLYCYRRHIZA GLABRA (LICORICE) ROOT EXTRACT - KIGELIA AFRICANA FRUIT EXTRACT - DIOSCOREA VILLOSA (WILD YAM) ROOT EXTRACT - EQUISETUM GIGANTEUM EXTRACT - CETYL PEG/PPG-10/1 DIMETHICONE - DIMETHICONE/VINYL DIMETHICONE CROSSPOLYMER - TRIETHOXYCAPRYLYLSILANE - SYNTHETIC FLUORPHLOGOPITE - STEARIC ACID - ALUMINA - GLYCERYL CAPRYLATE - PALMITIC ACID - CAPRYLYL GLYCOL - ALUMINUM HYDROXIDE - PENTAERYTHRITYL TETRA-DI-T-BUTYL HYDROXYHYDROCINNAMATE - TIN OXIDE - ALCOHOL - ETHYLHEXYLGLYCERIN - PARFUM/FRAGRANCE - HEXYL CINNAMAL - ALPHA-ISOMETHYL IONONE - LINALOOL - CITRONELLOL – GERANIOL

Questions or comments?

Call toll free 1-888-975-2162